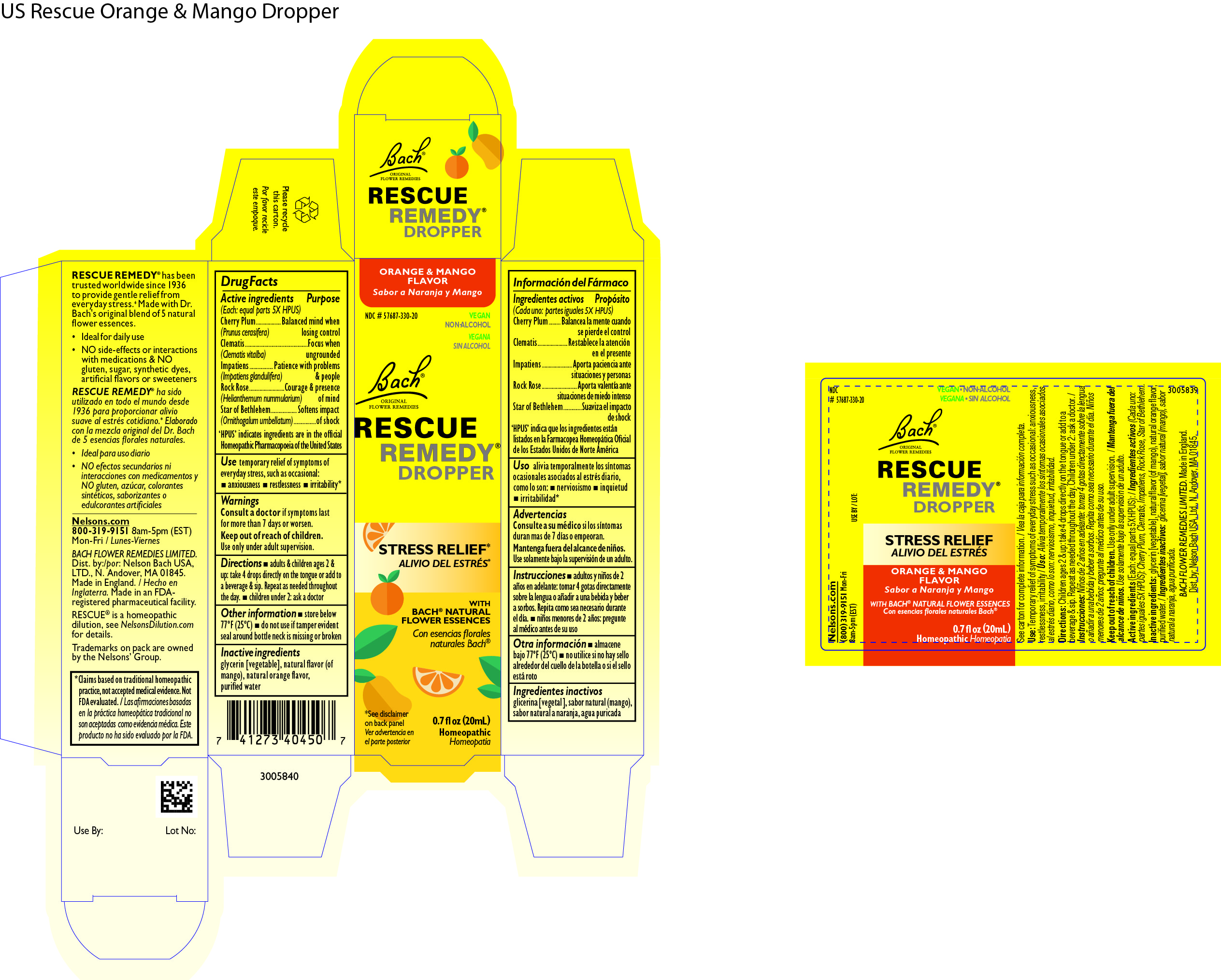 DRUG LABEL: Rescue Remedy Dropper Orange and Mango
NDC: 57687-330 | Form: SOLUTION/ DROPS
Manufacturer: Nelson Bach USA Limited
Category: homeopathic | Type: HUMAN OTC DRUG LABEL
Date: 20240625

ACTIVE INGREDIENTS: PRUNUS CERASIFERA FLOWER 5 [hp_X]/0.095 mL; IMPATIENS GLANDULIFERA FLOWER 5 [hp_X]/0.095 mL; HELIANTHEMUM NUMMULARIUM FLOWER 5 [hp_X]/0.095 mL; CLEMATIS VITALBA FLOWER 5 [hp_X]/0.095 mL; ORNITHOGALUM UMBELLATUM FLOWERING TOP 5 [hp_X]/0.095 mL
INACTIVE INGREDIENTS: MANGO; WATER; GLYCERIN; ORANGE

Rescue Remedy Dropper Orange & Mango

Drug Facts - Active Ingredients

Drug Facts

Active ingredients (Each: equal parts 5X HPUS)

Purpose

Cherry Plum
(Prunus cerasifera)

Balanced mind when losing control

Clematis
(Clematis vitalba)

Focus when ungrounded

Impatiens
(Impatiens glandulifera)

Patience with problems & people

Rock Rose
(Helianthemum nummularium)

Courage & presence of mind

Star of Bethlehem
(Ornithogalum umbellatum)

Softens impact of shock

'HPUS' indicates ingredients are in the official Homeopathic Pharmacopoeia of the United States

Use

temporary relief of symptoms of everyday stress, such as occasional:

anxiousness
restlessness
irritability 1

1

Claims based on traditional homeopathic practice, not accepted medical evidence. Not FDA evaluated.

Warnings

Consult a doctor if symptoms last for more than 7 days or worsen.

Keep out of reach of children

Use only under adult supervision

Directions

Adults & Children ages 2 & up
take 4 drops directly on the tongue or add to a beverage & sip. Repeat as needed throughout the day.
children under 2: ask a doctor before use

Other Information

store below 77°F (25°C)
do not use if tamper evident seal around bottle neck is missing or broken

Inactive Ingredients

glycerin [vegetable], natural flavour of mango, natural flavour of orange, purified water

Questions

(800) 319-9151 Mon-Fri 8am-5pm (EST)

Distributed by

Dist by

Nelson Bach USA Ltd, N Andover, MA 01845

OTC Purpose

For the relief of occasional stress

Keep out of reach of children

PACKAGE LABEL

Orange & Mango Flavour

NDC 57687-330-20

VEGAN
NON-ALCOHOL

Bach ®
ORIGINAL
FLOWER REMEDIES

RESCUE
REMEDY ®
DROPPER

STRESS
RELIEF*

WITH BACH ®
NATURAL
FLOWER
ESSENCES

0.7 fl oz (20mL)

HOMEOPATHIC

* See disclaimer on
side panel